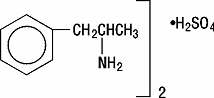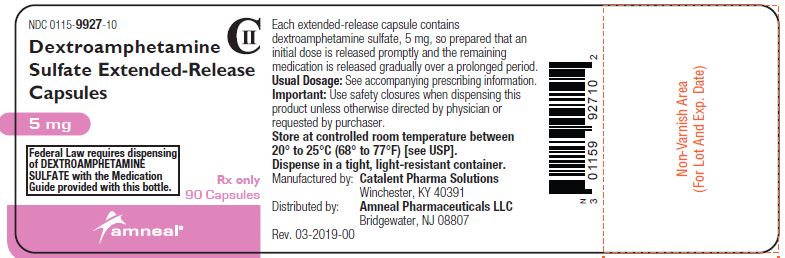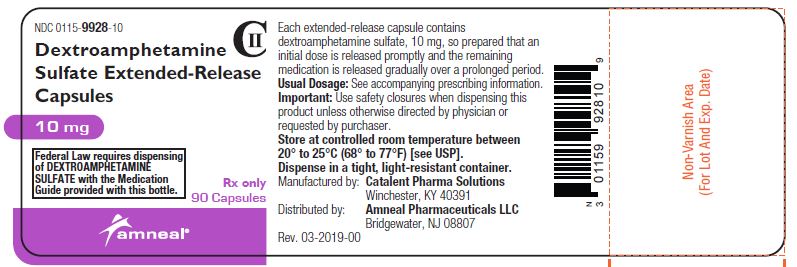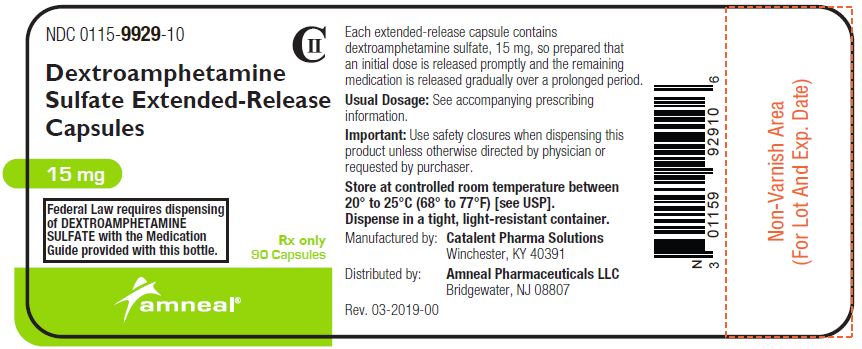 DRUG LABEL: Dextroamphetamine Sulfate
NDC: 0115-9927 | Form: CAPSULE, EXTENDED RELEASE
Manufacturer: Amneal Pharmaceuticals of New York LLC
Category: prescription | Type: HUMAN PRESCRIPTION DRUG LABEL
Date: 20231231
DEA Schedule: CII

ACTIVE INGREDIENTS: DEXTROAMPHETAMINE SULFATE 5 mg/1 1
INACTIVE INGREDIENTS: CETYL ALCOHOL; D&C YELLOW NO. 10; DIBUTYL SEBACATE; ETHYLCELLULOSE (100 MPA.S); FD&C RED NO. 40; FD&C YELLOW NO. 6; GELATIN; HYPROMELLOSES; POLYETHYLENE GLYCOL, UNSPECIFIED; POVIDONE; SODIUM LAURYL SULFATE; FD&C BLUE NO. 1

DEXTROAMPHETAMINE SULFATE EXTENDED-RELEASE CAPSULES, CII
Rx Only

WARNING

AMPHETAMINES HAVE A HIGH POTENTIAL FOR ABUSE. ADMINISTRATION OF AMPHETAMINES FOR PROLONGED PERIODS OF TIME MAY LEAD TO DRUG DEPENDENCE AND MUST BE AVOIDED. PARTICULAR ATTENTION SHOULD BE PAID TO THE POSSIBILITY OF SUBJECTS OBTAINING AMPHETAMINES FOR NON-THERAPEUTIC USE OR DISTRIBUTION TO OTHERS, AND THE DRUGS SHOULD BE PRESCRIBED OR DISPENSED SPARINGLY.
MISUSE OF AMPHETAMINES MAY CAUSE SUDDEN DEATH AND SERIOUS CARDIOVASCULAR ADVERSE EVENTS.

DESCRIPTION

Dextroamphetamine sulfate is the dextro isomer of the compound d,l-amphetamine sulfate, a sympathomimetic amine of the amphetamine group. Chemically, dextroamphetamine is d-alpha-methylphenethylamine, and is present in all forms of dextroamphetamine sulfate as the neutral sulfate.

Structural formula:

Each extended-release capsule is so prepared that an initial dose is released promptly and the remaining medication is released gradually over a prolonged period. Each capsule, with brown cap and natural body, contains 5 mg, 10 mg or 15 mg dextroamphetamine sulfate. The 5 mg capsule is imprinted in white with IX and 5 mg on the brown cap and is imprinted in white with 673 and 5 mg on the natural body. The 10 mg capsule is imprinted in white with IX and 10 mg on the brown cap and is imprinted in white with 674 and 10 mg on the natural body. The 15 mg capsule is imprinted in white with IX and 15 mg on the brown cap and is imprinted in white with 675 and 15 mg on the natural body. Product reformulation in 1996 has caused a minor change in the color of the time-released pellets within each capsule. Inactive ingredients now consist of cetyl alcohol, D&C Yellow No. 10, dibutyl sebacate, ethylcellulose, FD&C Blue No. 1, FD&C Red No. 40, FD&C Yellow No. 6, gelatin, hypromellose, polyethylene glycol, povidone, sodium lauryl sulfate, sugar spheres, and trace amounts of other inactive ingredients.

CLINICAL PHARMACOLOGY

Amphetamines are noncatecholamine, sympathomimetic amines with CNS stimulant activity. Peripheral actions include elevations of systolic and diastolic blood pressures and weak bronchodilator and respiratory stimulant action.

There is neither specific evidence that clearly establishes the mechanism whereby amphetamines produce mental and behavioral effects in children, nor conclusive evidence regarding how these effects relate to the condition of the central nervous system.

Dextroamphetamine sulfate extended-release capsules are formulated to release the active drug substance in vivo in a more gradual fashion than the standard formulation, as demonstrated by blood levels. The formulation has not been shown superior in effectiveness over the same dosage of the standard, non-controlled-release formulations given in divided doses.

Pharmacokinetics

The pharmacokinetics of the tablet and extended-release capsule were compared in 12 healthy subjects. The extent of bioavailability of the extended-release capsule was similar compared to the immediate-release tablet. Following administration of three 5-mg tablets, average maximal dextroamphetamine plasma concentrations (Cmax) of 36.6 ng/mL were achieved at approximately 3 hours. Following administration of one 15-mg extended-release capsule, maximal dextroamphetamine plasma concentrations were obtained approximately 8 hours after dosing. The average Cmax was 23.5 ng/mL. The average plasma T½ was similar for both the tablet and extended-release capsule and was approximately 12 hours.

In 12 healthy subjects, the rate and extent of dextroamphetamine absorption were similar following administration of the extended-release capsule formulation in the fed (58 g to 75 g fat) and fasted state.

INDICATIONS AND USAGE

Dextroamphetamine sulfate is indicated in:

Narcolepsy

Attention Deficit Disorder with Hyperactivity

As an integral part of a total treatment program that typically includes other measures (psychological, educational, social) for patients (ages 6 years to 16 years) with this syndrome. A diagnosis of Attention Deficit Hyperactivity Disorder (ADHD; DSM-IV) implies the presence of hyperactive-impulsive or inattentive symptoms that caused impairment and were present before age 7 years. The symptoms must cause clinically significant impairment, e.g., in social, academic, or occupational functioning, and be present in 2 or more settings, e.g., school (or work) and at home. The symptoms must not be better accounted for by another mental disorder. For the Inattentive Type, at least 6 of the following symptoms must have persisted for at least 6 months: lack of attention to details/careless mistakes; lack of sustained attention; poor listener; failure to follow through on tasks; poor organization; avoids tasks requiring sustained mental effort; loses things; easily distracted; forgetful. For the Hyperactive-Impulsive Type, at least 6 of the following symptoms must have persisted for at least 6 months: fidgeting/squirming; leaving seat; inappropriate running/climbing; difficulty with quiet activities; “on the go”; excessive talking; blurting answers; can’t wait turn; intrusive. The Combined Type requires both inattentive and hyperactive-impulsive criteria to be met.

Special Diagnostic Considerations

Specific etiology of this syndrome is unknown, and there is no single diagnostic test. Adequate diagnosis requires the use of medical and special psychological, educational, and social resources. Learning may or may not be impaired. The diagnosis must be based upon a complete history and evaluation of the patient and not solely on the presences of the required number of DSM-IV characteristics.

Need for Comprehensive Treatment Program

Dextroamphetamine sulfate is indicated as an integral part of a total treatment program for ADHD that may include other measures (psychological, educational, social) for patients with this syndrome. Drug treatment may not be indicated for all patients with this syndrome. Stimulants are not intended for use in patients who exhibit symptoms secondary to environmental factors and/or other primary psychiatric disorders, including psychosis. Appropriate educational placement is essential and psychosocial intervention is often helpful. When remedial measures alone are insufficient, the decision to prescribe stimulant medication will depend upon the physician’s assessment of the chronicity and severity of the patient’s symptoms.

CONTRAINDICATIONS

Advanced arteriosclerosis, symptomatic cardiovascular disease, moderate to severe hypertension, hyperthyroidism, known hypersensitivity or idiosyncrasy to the sympathomimetic amines, glaucoma.

Agitated states.

Patients with a history of drug abuse.

Known hypersensitivity or idiosyncrasy to amphetamine.

In patients known to be hypersensitive to amphetamine, or other components of dextroamphetamine sulfate. Hypersensitivity reactions such as angioedema and anaphylactic reactions have been reported in patients treated with other amphetamine products [see Adverse Reactions].

Patients taking monoamine oxidase inhibitors (MAOIs), or within 14 days of stopping MAOIs (including MAOIs such as linezolid or intravenous methylene blue), because of an increased risk of hypertensive crisis [see Warnings and Drug Interactions].

WARNINGS

Serious Cardiovascular Events

Sudden Death in Patients with Pre-existing Structural Cardiac Abnormalities or Other Serious Heart Problems

Children and Adolescents

Sudden death has been reported in association with CNS stimulant treatment at usual doses in children and adolescents with structural cardiac abnormalities or other serious heart problems. Although some serious heart problems alone carry an increased risk of sudden death, stimulant products generally should not be used in children or adolescents with known serious structural cardiac abnormalities, cardiomyopathy, serious heart rhythm abnormalities, or other serious cardiac problems that may place them at increased vulnerability to the sympathomimetic effects of a stimulant drug.

Adults

Sudden deaths, stroke, and myocardial infarction have been reported in adults taking stimulant drugs at usual doses for ADHD. Although the role of stimulants in these adult cases is also unknown, adults have a greater likelihood than children of having serious structural cardiac abnormalities, cardiomyopathy, serious heart rhythm abnormalities, coronary artery disease, or other serious cardiac problems. Adults with such abnormalities should also generally not be treated with stimulant drugs [see Contraindications].

Hypertension and Other Cardiovascular Conditions

Stimulant medications cause a modest increase in average blood pressure (about 2 mmHg to 4 mmHg) and average heart rate (about 3 bpm to 6 bpm), and individuals may have larger increases. While the mean changes alone would not be expected to have short-term consequences, all patients should be monitored for larger changes in heart rate and blood pressure. Caution is indicated in treating patients whose underlying medical conditions might be compromised by increases in blood pressure or heart rate, e.g., those with pre-existing hypertension, heart failure, recent myocardial infarction, or ventricular arrhythmia [see Contraindications].

Assessing Cardiovascular Status in Patients Being Treated with Stimulant Medications

Children, adolescents, or adults who are being considered for treatment with stimulant medications should have a careful history (including assessment for a family history of sudden death or ventricular arrhythmia) and physical exam to assess for the presence of cardiac disease, and should receive further cardiac evaluation if findings suggest such disease (e.g., electrocardiogram and echocardiogram). Patients who develop symptoms such as exertional chest pain, unexplained syncope, or other symptoms suggestive of cardiac disease during stimulant treatment should undergo a prompt cardiac evaluation.

Psychiatric Adverse Events

Pre-Existing Psychosis

Administration of stimulants may exacerbate symptoms of behavior disturbance and thought disorder in patients with a pre-existing psychotic disorder.

Bipolar Illness

Particular care should be taken in using stimulants to treat ADHD in patients with comorbid bipolar disorder because of concern for possible induction of a mixed/manic episode in such patients. Prior to initiating treatment with a stimulant, patients with comorbid depressive symptoms should be adequately screened to determine if they are at risk for bipolar disorder; such screening should include a detailed psychiatric history, including a family history of suicide, bipolar disorder, and depression.

Emergence of New Psychotic or Manic Symptoms

Treatment emergent psychotic or manic symptoms, e.g., hallucinations, delusional thinking, or mania in children and adolescents without a prior history of psychotic illness or mania can be caused by stimulants at usual doses. If such symptoms occur, consideration should be given to a possible causal role of the stimulant, and discontinuation of treatment may be appropriate. In a pooled analysis of multiple short-term, placebo-controlled studies, such symptoms occurred in about 0.1% (4 patients with events out of 3,482 exposed to methylphenidate or amphetamine for several weeks at usual doses) of stimulant-treated patients compared to 0 in placebo-treated patients.

Aggression

Aggressive behavior or hostility is often observed in children and adolescents with ADHD, and has been reported in clinical trials and the postmarketing experience of some medications indicated for the treatment of ADHD. Although there is no systematic evidence that stimulants cause aggressive behavior or hostility, patients beginning treatment for ADHD should be monitored for the appearance of, or worsening of, aggressive behavior or hostility.

Long-Term Suppression of Growth

Careful follow-up of weight and height in children ages 7 to 10 years who were randomized to either methylphenidate or non-medication treatment groups over 14 months, as well as in naturalistic subgroups of newly methylphenidate-treated and non-medication treated children older than 36 months (to the ages of 10 to 13 years), suggests that consistently medicated children (i.e. treatment for 7 days per week throughout the year) have a temporary slowing in growth rate (on average, a total of about 2 cm less growth in height and 2.7 kg less growth in weight over 3 years), without evidence of growth rebound during this period of development. Published data are inadequate to determine whether chronic use of amphetamines may cause a similar suppression of growth, however, it is anticipated that they likely have this effect as well. Therefore, growth should be monitored during treatment with stimulants, and patients who are not growing or gaining height or weight as expected may need to have their treatment interrupted.

Seizures

There is some clinical evidence that stimulants may lower the convulsive threshold in patients with prior history of seizures, in patients with prior EEG abnormalities in absence of seizures, and, very rarely, in patients without a history of seizures and no prior EEG evidence of seizures. In the presence of seizures, the drug should be discontinued.

Peripheral Vasculopathy, including Raynaud’s phenomenon

Stimulants, including dextroamphetamine sulfate, used to treat ADHD are associated with peripheral vasculopathy, including Raynaud’s phenomenon. Signs and symptoms are usually intermittent and mild; however, very rare sequelae include digital ulceration and/or soft tissue breakdown. Effects of peripheral vasculopathy, including Raynaud’s phenomenon, were observed in post-marketing reports at different times and at therapeutic doses in all age groups throughout the course of treatment. Signs and symptoms generally improve after reduction in dose or discontinuation of drug. Careful observation for digital changes is necessary during treatment with ADHD stimulants. Further clinical evaluation (e.g., rheumatology referral) may be appropriate for certain patients.

Serotonin Syndrome

Serotonin syndrome, a potentially life-threatening reaction, may occur when amphetamines are used in combination with other drugs that affect the serotonergic neurotransmitter systems such as monoamine oxidase inhibitors (MAOIs), selective serotonin reuptake inhibitors (SSRIs), serotonin norepinephrine reuptake inhibitors (SNRIs), triptans, tricyclic antidepressants, fentanyl, lithium, tramadol, tryptophan, buspirone, and St. John’s Wort [see Drug Interactions]. Amphetamines and amphetamine derivatives are known to be metabolized, to some degree, by cytochrome P450 2D6 (CYP2D6) and display minor inhibition of CYP2D6 metabolism [see Clinical Pharmacology]. The potential for a pharmacokinetic interaction exists with the co-administration of CYP2D6 inhibitors which may increase the risk with increased exposure to dextroamphetamine sulfate. In these situations, consider an alternative non-serotonergic drug or an alternative drug that does not inhibit CYP2D6 [see Drug Interactions].

Serotonin syndrome symptoms may include mental status changes (e.g., agitation, hallucinations, delirium, and coma), autonomic instability (e.g., tachycardia, labile blood pressure, dizziness, diaphoresis, flushing, hyperthermia), neuromuscular symptoms (e.g., tremor, rigidity, myoclonus, hyperreflexia, incoordination), seizures, and/or gastrointestinal symptoms (e.g., nausea, vomiting, diarrhea).

Concomitant use of dextroamphetamine sulfate with MAOI drugs is contraindicated [see Contraindications].

Discontinue treatment with dextroamphetamine sulfate and any concomitant serotonergic agents immediately if the above symptoms occur, and initiate supportive symptomatic treatment. If concomitant use of dextroamphetamine sulfate with other serotonergic drugs or CYP2D6 inhibitors is clinically warranted, initiate dextroamphetamine sulfate with lower doses, monitor patients for the emergence of serotonin syndrome during drug initiation or titration, and inform patients of the increased risk for serotonin syndrome.

Visual Disturbance

Difficulties with accommodation and blurring of vision have been reported with stimulant treatment.

PRECAUTIONS

General

The least amount feasible should be prescribed or dispensed at 1 time in order to minimize the possibility of overdosage.

Information for Patients

Amphetamines may impair the ability of the patient to engage in potentially hazardous activities such as operating machinery or vehicles; the patient should therefore be cautioned accordingly.

Prescribers or other health professionals should inform patients, their families, and their caregivers about the benefits and risks associated with treatment with dextroamphetamine and should counsel them in its appropriate use. A patient Medication Guide is available for dextroamphetamine sulfate extended-release capsules. The prescriber or health professional should instruct patients, their families, and their caregivers to read the Medication Guide and should assist them in understanding its contents. Patients should be given the opportunity to discuss the contents of the Medication Guide and to obtain answers to any questions they may have. The complete text of the Medication Guide is reprinted at the end of this document.

Circulation problems in fingers and toes [Peripheral vasculopathy, including Raynaud’s phenomenon]

- Instruct patients beginning treatment with dextroamphetamine sulfate about the risk of peripheral vasculopathy, including Raynaud’s phenomenon, and associated signs and symptoms: fingers or toes may feel numb, cool, painful, and/or may change color from pale, to blue, to red.
- Instruct patients to report to their physician any new numbness, pain, skin color change, or sensitivity to temperature in fingers or toes.
- Instruct patients to call their physician immediately with any signs of unexplained wounds appearing on fingers or toes while taking dextroamphetamine sulfate.
- Further clinical evaluation (e.g., rheumatology referral) may be appropriate for certain patients.

Drug Interactions

Acidifying Agents

Lower blood levels and efficacy of amphetamines. Increase dose based on clinical response. Examples of acidifying agents include gastrointestinal acidifying agents (e.g., guanethidine, reserpine, glutamic acid hydrochloride, ascorbic acid) and urinary acidifying agents (e.g., ammonium chloride, sodium acid phosphate, methenamine salts).

Adrenergic Blockers

Adrenergic blockers are inhibited by amphetamines.

Alkalinizing Agents

Increase blood levels and potentiate the action of amphetamine. Co-administration of dextroamphetamine sulfate and gastrointestinal alkalinizing agents should be avoided. Examples of alkalinizing agents include gastrointestinal alkalinizing agents (e.g., sodium bicarbonate) and urinary alkalinizing agents (e.g. acetazolamide, some thiazides).

Tricyclic Antidepressants

May enhance the activity of tricyclic or sympathomimetic agents causing striking and sustained increases in the concentration of d-amphetamine in the brain; cardiovascular effects can be potentiated. Monitor frequently and adjust or use alternative therapy based on clinical response. Examples of tricyclic antidepressants include desipramine, protriptyline.

CYP2D6 Inhibitors

The concomitant use of dextroamphetamine sulfate and CYP2D6 inhibitors may increase the exposure of dextroamphetamine sulfate compared to the use of the drug alone and increase the risk of serotonin syndrome. Initiate with lower doses and monitor patients for signs and symptoms of serotonin syndrome particularly during dextroamphetamine sulfate initiation and after a dosage increase. If serotonin syndrome occurs, discontinue dextroamphetamine sulfate and the CYP2D6 inhibitor [see Warnings, Overdosage]. Examples of CYP2D6 Inhibitors include paroxetine and fluoxetine (also serotonergic drugs), quinidine, ritonavir.

Serotonergic Drugs

The concomitant use of dextroamphetamine sulfate and serotonergic drugs increases the risk of serotonin syndrome. Initiate with lower doses and monitor patients for signs and symptoms of serotonin syndrome, particularly during dextroamphetamine sulfate initiation or dosage increase. If serotonin syndrome occurs, discontinue dextroamphetamine sulfate and the concomitant serotonergic drug(s) [see Warnings and Precautions]. Examples of serotonergic drugs include selective serotonin reuptake inhibitors (SSRI), serotonin norepinephrine reuptake inhibitors (SNRI), triptans, tricyclic antidepressants, fentanyl, lithium, tramadol, tryptophan, buspirone, St. John’s Wort.

MAO Inhibitors

Concomitant use of MAOIs and CNS stimulants can cause hypertensive crisis. Potential outcomes include death, stroke, myocardial infarction, aortic dissection, ophthalmological complications, eclampsia, pulmonary edema, and renal failure. Do not administer dextroamphetamine sulfate concomitantly or within 14 days after discontinuing MAOI [see Contraindications and Warnings]. Examples of MAOIs include selegiline, tranylcypromine, isocarboxazid, phenelzine, linezolid, methylene blue.

Proton Pump Inhibitors

Time to maximum concentration (Tmax) of amphetamine is decreased compared to when administered alone. Monitor patients for changes in clinical effect and adjust therapy based on clinical response. An example of a proton pump inhibitor is omeprazole.

Antihistamines

Amphetamines may counteract the sedative effect of antihistamines.

Antihypertensives

Amphetamines may antagonize the hypotensive effects of antihypertensives.

Chlorpromazine

Chlorpromazine blocks dopamine and norepinephrine reuptake, thus inhibiting the central stimulant effects of amphetamines, and can be used to treat amphetamine poisoning.

Ethosuximide

Amphetamines may delay intestinal absorption of ethosuximide.

Haloperidol

Haloperidol blocks dopamine and norepinephrine reuptake, thus inhibiting the central stimulant effects of amphetamines.

Lithium Carbonate

The stimulatory effects of amphetamines may be inhibited by lithium carbonate.

Meperidine

Amphetamines potentiate the analgesic effect of meperidine.

Methenamine Therapy

Urinary excretion of amphetamines is increased, and efficacy is reduced, by acidifying agents used in methenamine therapy.

Norepinephrine

Amphetamines enhance the adrenergic effect of norepinephrine.

Phenobarbital

Amphetamines may delay intestinal absorption of phenobarbital; co-administration of phenobarbital may produce a synergistic anticonvulsant action.

Phenytoin

Amphetamines may delay intestinal absorption of phenytoin; co-administration of phenytoin may produce a synergistic anticonvulsant action.

Propoxyphene

In cases of propoxyphene overdosage, amphetamine CNS stimulation is potentiated and fatal convulsions can occur.

Veratrum Alkaloids

Amphetamines inhibit the hypotensive effect of veratrum alkaloids.

Drug/Laboratory Test Interactions

Amphetamines can cause a significant elevation in plasma corticosteroid levels. This increase is greatest in the evening.

Amphetamines may interfere with urinary steroid determinations.

Carcinogenesis/Mutagenesis

Mutagenicity studies and long-term studies in animals to determine the carcinogenic potential of dextroamphetamine sulfate have not been performed.

Pregnancy

Teratogenic Effects

Dextroamphetamine sulfate has been shown to have embryotoxic and teratogenic effects when administered to A/Jax mice and C57BL mice in doses approximately 41 times the maximum human dose. Embryotoxic effects were not seen in New Zealand white rabbits given the drug in doses 7 times the human dose nor in rats given 12.5 times the maximum human dose. While there are no adequate and well-controlled studies in pregnant women, there has been 1 report of severe congenital bony deformity, tracheoesophageal fistula, and anal atresia (VATER association) in a baby born to a woman who took dextroamphetamine sulfate with lovastatin during the first trimester of pregnancy. Dextroamphetamine sulfate should be used during pregnancy only if the potential benefit justifies the potential risk to the fetus.

Nonteratogenic Effects

Infants born to mothers dependent on amphetamines have an increased risk of premature delivery and low birth weight. Also, these infants may experience symptoms of withdrawal as demonstrated by dysphoria, including agitation, and significant lassitude.

Nursing Mothers

Amphetamines are excreted in human milk. Mothers taking amphetamines should be advised to refrain from nursing.

Pediatric Use

Long-term effects of amphetamines in pediatric patients have not been well established.

Dextroamphetamine sulfate is not recommended for use in pediatric patients younger than 6 years of age with Attention Deficit Disorder with Hyperactivity described under INDICATIONS AND USAGE.

Clinical experience suggests that in psychotic children, administration of amphetamines may exacerbate symptoms of behavior disturbance and thought disorder.

Amphetamines have been reported to exacerbate motor and phonic tics and Tourette’s syndrome. Therefore, clinical evaluation for tics and Tourette’s syndrome in children and their families should precede use of stimulant medications.

Data are inadequate to determine whether chronic administration of amphetamines may be associated with growth inhibition; therefore, growth should be monitored during treatment.

Drug treatment is not indicated in all cases of Attention Deficit Disorder with Hyperactivity and should be considered only in light of the complete history and evaluation of the child. The decision to prescribe amphetamines should depend on the physician’s assessment of the chronicity and severity of the child’s symptoms and their appropriateness for his or her age. Prescription should not depend solely on the presence of one or more of the behavioral characteristics.

When these symptoms are associated with acute stress reactions, treatment with amphetamines is usually not indicated.

ADVERSE REACTIONS

Cardiovascular

Palpitations, tachycardia, elevation of blood pressure. There have been isolated reports of cardiomyopathy associated with chronic amphetamine use.

Central Nervous System

Psychotic episodes at recommended doses (rare), overstimulation, restlessness, dizziness, insomnia, euphoria, dyskinesia, dysphoria, tremor, headache, exacerbation of motor and phonic tics, and Tourette’s syndrome.

Gastrointestinal

Dryness of the mouth, unpleasant taste, diarrhea, constipation, other gastrointestinal disturbances. Anorexia and weight loss may occur as undesirable effects.

Allergic

Urticaria.

Endocrine

Impotence, changes in libido, frequent or prolonged erections.

Musculoskeletal

Rhabdomyolysis.

Skin and Subcutaneous Tissue Disorders

Alopecia.

To report SUSPECTED ADVERSE REACTIONS, contact Amneal Pharmaceuticals at 1-877-835-5472 or FDA at 1-800-FDA-1088 or www.fda.gov/medwatch.

DRUG ABUSE AND DEPENDENCE

Dextroamphetamine sulfate is a Schedule II controlled substance.
Amphetamines have been extensively abused. Tolerance, extreme psychological dependence and severe social disability have occurred. There are reports of patients who have increased the dosage to many times that recommended. Abrupt cessation following prolonged high dosage administration results in extreme fatigue and mental depression; changes are also noted on the sleep EEG.

Manifestations of chronic intoxication with amphetamines include severe dermatoses, marked insomnia, irritability, hyperactivity, and personality changes. The most severe manifestation of chronic intoxication is psychosis, often clinically indistinguishable from schizophrenia. This is rare with oral amphetamines.

OVERDOSAGE

Manifestations of amphetamine overdose include restlessness, tremor, hyperreflexia, rapid respiration, confusion, assaultiveness, hallucinations, panic states, hyperpyrexia and rhabdomyolysis. Fatigue and depression usually follow the central nervous system stimulation. Serotonin syndrome has also been reported. Cardiovascular effects include arrhythmias, hypertension or hypotension and circulatory collapse. Gastrointestinal symptoms include nausea, vomiting, diarrhea and abdominal cramps. Fatal poisoning is usually preceded by convulsions and coma.

Treatment

Consult with a Certified Poison Control Center for up to date guidance and advice.

TREATMENT

Consult with a Certified Poison Control Center for up-to-date guidance and advice. Management of acute amphetamine intoxication is largely symptomatic and includes gastric lavage, administration of activated charcoal, administration of a cathartic, and sedation. Experience with hemodialysis or peritoneal dialysis is inadequate to permit recommendation in this regard. Acidification of the urine increases amphetamine excretion, but is believed to increase risk of acute renal failure if myoglobinuria is present. If acute, severe hypertension complicates amphetamine overdosage, administration of intravenous phentolamine (Bedford Laboratories) has been suggested. However, a gradual drop in blood pressure will usually result when sufficient sedation has been achieved.

Chlorpromazine antagonizes the central stimulant effects of amphetamines and can be used to treat amphetamine intoxication.

Since much of the extended-release capsule medication is coated for gradual release, therapy directed at reversing the effects of the ingested drug and at supporting the patient should be continued for as long as overdosage symptoms remain. Saline cathartics are useful for hastening the evacuation of pellets that have not already released medication.

DOSAGE AND ADMINISTRATION

Amphetamines should be administered at the lowest effective dosage and dosage should be individually adjusted. Late evening doses should be avoided because of the resulting insomnia.

Narcolepsy

Usual dose is 5 to 60 mg per day in divided doses, depending on the individual patient response.

Narcolepsy seldom occurs in children under 12 years of age; however, when it does, dextroamphetamine sulfate may be used. The suggested initial dose for patients aged 6 to 12 is 5 mg daily; daily dose may be raised in increments of 5 mg at weekly intervals until an optimal response is obtained. In patients 12 years of age and older, start with 10 mg daily; daily dosage may be raised in increments of 10 mg at weekly intervals until an optimal response is obtained. If bothersome adverse reactions appear (e.g., insomnia or anorexia), dosage should be reduced. Extended-release capsules may be used for once-a-day dosage wherever appropriate.

Attention Deficit Disorder with Hyperactivity

The extended-release capsule formulation is not recommended for pediatric patients younger than 6 years of age.

In pediatric patients 6 years of age and older, start with 5 mg once or twice daily; daily dosage may be raised in increments of 5 mg at weekly intervals until optimal response is obtained.

Only in rare cases will it be necessary to exceed a total of 40 mg per day. Extended-release capsules may be used for once-a-day dosage wherever appropriate.

Where possible, drug administration should be interrupted occasionally to determine if there is a recurrence of behavioral symptoms sufficient to require continued therapy.

HOW SUPPLIED

Dextroamphetamine Sulfate Extended-Release Capsules are supplied as follows:
Dextroamphetamine Sulfate Extended-Release Capsules, 5 mg: Each capsule, with brown cap and natural body, contains dextroamphetamine sulfate. The 5 mg capsule is imprinted in white with IX and 5 mg on the brown cap and is imprinted in white with 673 and 5 mg on the natural body.
They are available as:
Bottles of 90: NDC 0115-9927-10
Dextroamphetamine Sulfate Extended-Release Capsules, 10 mg: Each capsule, with brown cap and natural body, contains dextroamphetamine sulfate. The 10 mg capsule is imprinted in white with IX and 10 mg on the brown cap and is imprinted in white with 674 and 10 mg on the natural body.
They are available as:
Bottles of 90: NDC 0115-9928-10
Dextroamphetamine Sulfate Extended-Release Capsules, 15 mg: Each capsule, with brown cap and natural body, contains dextroamphetamine sulfate. The 15 mg capsule is imprinted in white with IX and 15 mg on the brown cap and is imprinted in white with 675 and 15 mg on the natural body.
They are available as:
Bottles of 90: NDC 0115-9929-10
Store at controlled room temperature between 20° to 25°C (68° to 77°F) [See USP].
Dispense in a tight, light-resistant container.
Manufactured by:
Catalent Pharma Solutions
Winchester, KY 40391
Distributed by:
Amneal Pharmaceuticals LLC
Bridgewater, NJ 08807
Rev. 03-2019-00
For additional copies of the printed medication guide, please visit www.amneal.com or contact us at 1-877-835-5472.

MEDICATION GUIDE

Dextroamphetamine Sulfate (dex” troe am fet’ a meen sul’ fate) Extended-Release Capsules, CII
Read the Medication Guide that comes with dextroamphetamine sulfate extended-release capsules before you or your child starts taking it and each time you get a refill. There may be new information. This Medication Guide does not take the place of talking to your doctor about your or your child’s treatment with dextroamphetamine sulfate extended-release capsules.

What is the most important information I should know about dextroamphetamine sulfate extended-release capsules?
The following have been reported with use of dextroamphetamine sulfate extended-release capsules and other stimulant medicines.
1. Heart-related problems:

- Sudden death in patients who have heart problems or heart defects
- Stroke and heart attack in adults
- Increased blood pressure and heart rate

Tell your doctor if you or your child has any heart problems, heart defects, high blood pressure, or a family history of these problems.
Your doctor should check you or your child carefully for heart problems before starting dextroamphetamine sulfate extended-release capsules.
Your doctor should check your or your child’s blood pressure and heart rate regularly during treatment with dextroamphetamine sulfate extended-release capsules.
Call your doctor right away if you or your child has any signs of heart problems such as chest pain, shortness of breath, or fainting while taking dextroamphetamine sulfate extended-release capsules.
2. Mental (Psychiatric) problems:
All Patients

- new or worse behavior and thought problems
- new or worse bipolar illness
- new or worse aggressive behavior or hostility

Children and Teenagers

- new psychotic symptoms (such as hearing voices, believing things that are not true, are suspicious) or new manic symptoms

Tell your doctor about any mental problems you or your child have, or about a family history of suicide, bipolar illness, or depression.
Call your doctor right away if you or your child has any new or worsening mental symptoms or problems while taking dextroamphetamine sulfate extended-release capsules, especially seeing or hearing things that are not real, believing things that are not real, or are suspicious.
3. Circulation problems in fingers and toes [Peripheral vasculopathy, including Raynaud’s phenomenon]:

- fingers or toes may feel numb, cool, painful
- fingers or toes may change color from pale, to blue, to red

Tell your doctor if you have or your child has numbness, pain, skin color change, or sensitivity to temperature in your fingers or toes.

Call your doctor right away if you have or your child has any signs of unexplained wounds appearing on fingers or toes while taking dextroamphetamine sulfate.

What are dextroamphetamine sulfate extended-release capsules?
Dextroamphetamine sulfate extended-release capsules are a central nervous system stimulant prescription medicine. It is used for the treatment of Attention-Deficit Hyperactivity Disorder (ADHD).
Dextroamphetamine sulfate extended-release capsules may help increase attention and decrease impulsiveness and hyperactivity in patients with ADHD.
Dextroamphetamine sulfate extended-release capsules should be used as a part of a total treatment program for ADHD that may include counselling or other therapies.
Dextroamphetamine sulfate extended-release capsules are also used in the treatment of a sleep disorder called narcolepsy.

Dextroamphetamine sulfate is a federally controlled substance (CII) because it can be abused or lead to dependence. Keep dextroamphetamine sulfate extended-release capsules in a safe place to prevent misuse and abuse. Selling or giving away dextroamphetamine sulfate extended-release capsules may harm others and is against the law.

Tell your doctor if you or your child have (or have a family history of) ever abused or been dependent on alcohol, prescription medicines or street drugs.

Who should not take dextroamphetamine sulfate extended-release capsules?
Dextroamphetamine sulfate extended-release capsules should not be taken if you or your child:

- Have heart disease or hardening of the arteries
- Have moderate to severe high blood pressure
- Have hyperthyroidism
- Have an eye problem called glaucoma
- Are very anxious, tense, or agitated
- Have a history of drug abuse
- Are taking or have taken within the past 14 days an antidepression medicine called a monoamine oxidase inhibitor or MAOI
- Is sensitive to, allergic to, or had a reaction to other stimulant medicines

Dextroamphetamine sulfate extended-release capsules are not recommended for use in children younger than 6 years old.
Dextroamphetamine sulfate extended-release capsules may not be right for you or your child. Before starting dextroamphetamine sulfate extended-release capsules tell your or your child’s doctor about all health conditions (or a family history of) including:

- Heart problems, heart defects, high blood pressure
- Mental problems including psychosis, mania, bipolar illness, or depression
- Tics or Tourette’s syndrome
- Thyroid problems
- Seizures or have had an abnormal brain wave test (EEG)
- Circulation problems in fingers and toes

Tell your doctor if you or your child is pregnant, planning to become pregnant, or breastfeeding.
Can dextroamphetamine sulfate extended-release capsules be taken with other medicines?
Tell your doctor about all of the medicines that you or your child takes including prescription and non-prescription medicines, vitamins, and herbal supplements.
Dextroamphetamine sulfate extended-release capsules and some medicines may interact with each other and cause serious side effects. Sometimes the doses of other medicines will need to be adjusted while taking dextroamphetamine sulfate extended-release capsules.
Your doctor will decide whether dextroamphetamine sulfate extended-release capsules can be taken with other medicines.
Especially tell your doctor if you or your child takes:

- Anti-depression medicines including MAOIs
- Blood pressure medicines
- Antacids
- Seizure medicines

Know the medicines that you or your child takes. Keep a list of your medicines with you to show your doctor and pharmacist.
Do not start any new medicine while taking dextroamphetamine sulfate extended-release capsules without talking to your doctor first.
How should dextroamphetamine sulfate extended-release capsules be taken?

- Take dextroamphetamine sulfate extended-release capsules exactly as prescribed. Your doctor may adjust the dose until it is right for you or your child.
- Dextroamphetamine sulfate extended-release capsules come as a capsule.
- Dextroamphetamine sulfate extended-release capsules are usually taken once a day in the morning. Dextroamphetamine sulfate extended-release capsules are extended-release capsules. It releases medicine into your body throughout the day.
- From time to time, your doctor may stop treatment with dextroamphetamine sulfate extended-release capsules for a while to check ADHD symptoms.
- Your doctor may do regular checks of the blood, heart, and blood pressure while taking dextroamphetamine sulfate extended-release capsules. Children should have their height and weight checked often while taking dextroamphetamine sulfate extended-release capsules. Treatment with dextroamphetamine sulfate extended-release capsules may be stopped if a problem is found during these check-ups.
- If you or your child takes too much dextroamphetamine sulfate extended-release capsules or overdoses, call your doctor or poison control center right away, or get emergency treatment.

What are possible side effects of dextroamphetamine sulfate extended-release capsules?
See “What is the most important information I should know about dextroamphetamine sulfate extended-release capsules?” for information on reported heart and mental problems.
Other serious side effects include:

- Slowing of growth (height and weight) in children
- Seizures, mainly in patients with a history of seizures
- Eyesight changes or blurred vision

Common side effects include:

- Fast heartbeat
- Decreased appetite
- Tremors
- Headache
- Trouble sleeping
- Dizziness
- Stomach upset
- Weight loss
- Dry mouth

Dextroamphetamine sulfate extended-release capsules may affect your or your child’s ability to drive or do other dangerous activities.
Talk to your doctor if you or your child has side effects that are bothersome or do not go away. This is not a complete list of possible side effects. Ask your doctor or pharmacist for more information. Call your doctor for medical advice about side effects. You may report side effects to FDA at 1-800-FDA-1088.
How should I store dextroamphetamine sulfate extended-release capsules?

- Store dextroamphetamine sulfate extended-release capsules in a safe place at room temperature, 68° to 77°F (20° to 25°C). Protect from light.
- Keep dextroamphetamine sulfate extended-release capsules and all medicines out of the reach of children.

General information about dextroamphetamine sulfate extended-release capsules
Medicines are sometimes prescribed for purposes other than those listed in a Medication Guide. Do not use dextroamphetamine sulfate extended-release capsules for a condition for which it was not prescribed. Do not give dextroamphetamine sulfate extended-release capsules to other people, even if they have the same condition. It may harm them and it is against the law.
This Medication Guide summarizes the most important information about dextroamphetamine sulfate extended-release capsules. If you would like more information, talk with your doctor. You can ask your doctor or pharmacist for information about dextroamphetamine sulfate extended-release capsules that was written for healthcare professionals. For more information about dextroamphetamine sulfate extended-release capsules, please contact Amneal Pharmaceuticals at 1-877-835-5472 or visit www.amneal.com.
What are the ingredients in dextroamphetamine sulfate extended-release capsules?
Active Ingredient: Dextroamphetamine sulfate
Inactive Ingredients: Cetyl alcohol, D&C Yellow No. 10, dibutyl sebacate, ethylcellulose, FD&C Blue No. 1, FD&C Red No. 40, FD&C Yellow No. 6, gelatin, hypromellose, polyethylene glycol, povidone, sodium lauryl sulfate, sugar spheres and trace amounts of other inactive ingredients.
This Medication Guide has been approved by the U.S. Food and Drug Administration.
Manufactured by:
Catalent Pharma Solutions
Winchester, KY 40391
Distributed by:
Amneal Pharmaceuticals LLC
Bridgewater, NJ 08807
Rev. 03-2019-00
For additional copies of the printed medication guide, please visit www.amneal.com or contact us at 1-877-835-5472.

PRINCIPAL DISPLAY PANEL - 10 mg BOTTLE LABEL

\